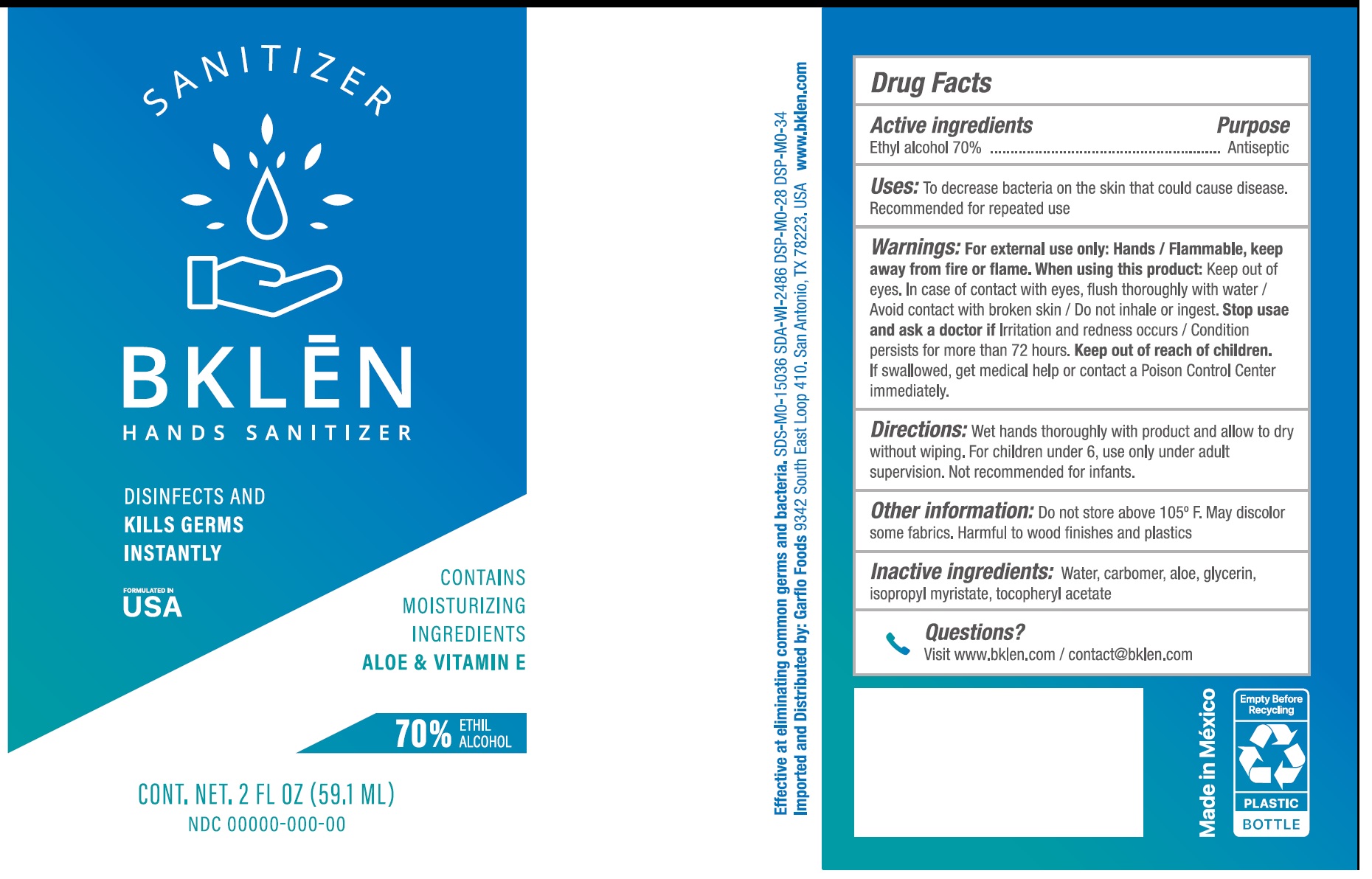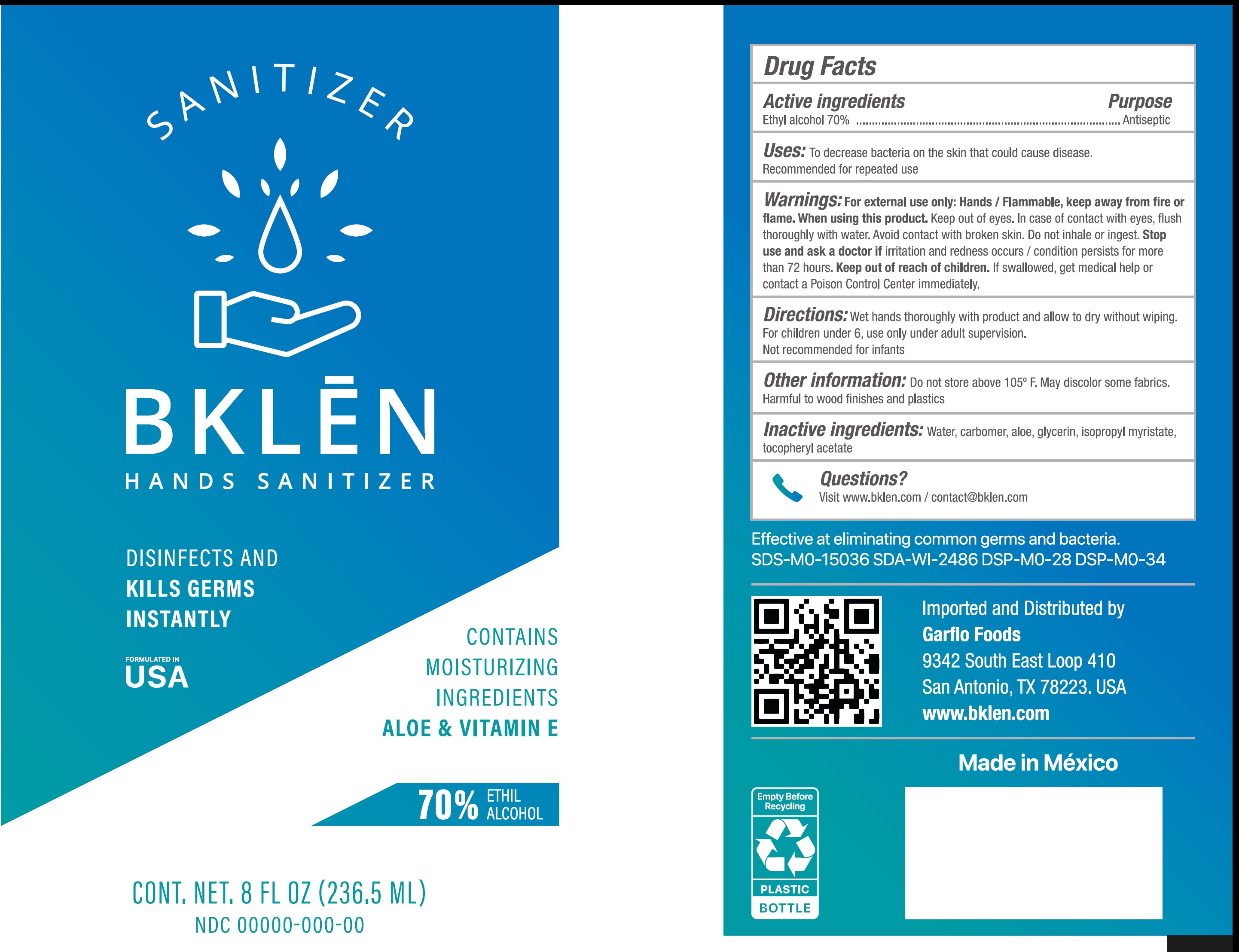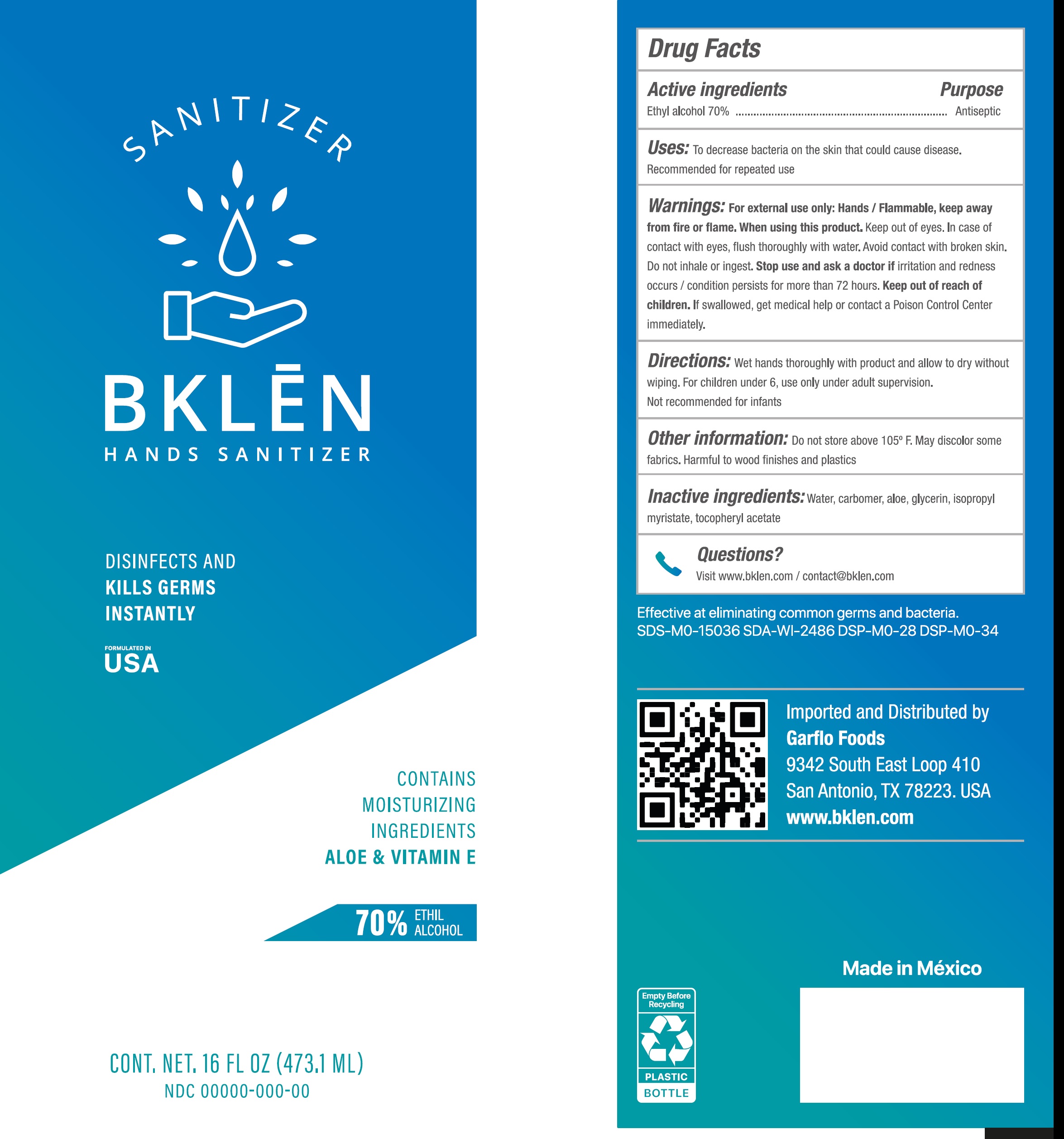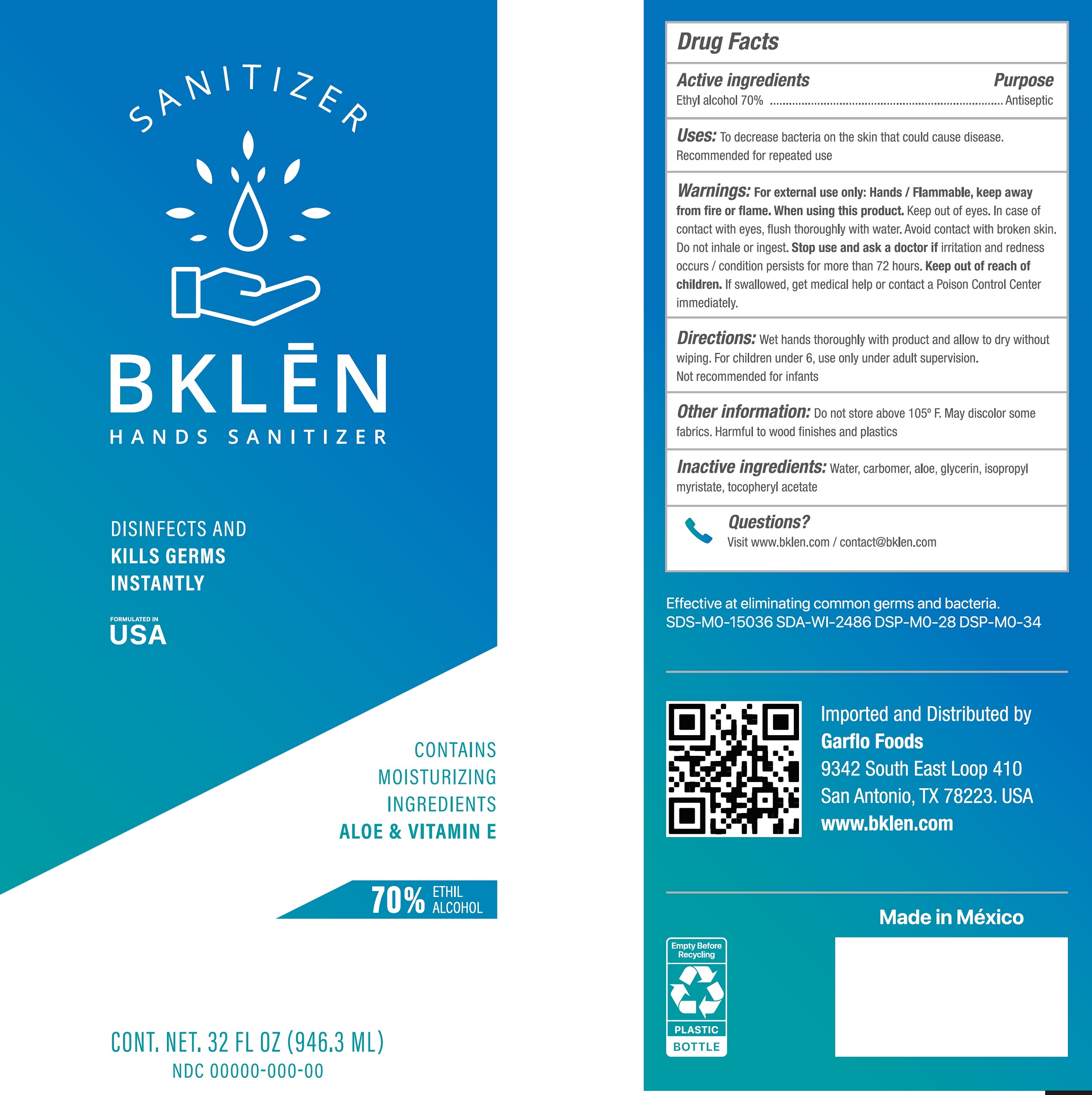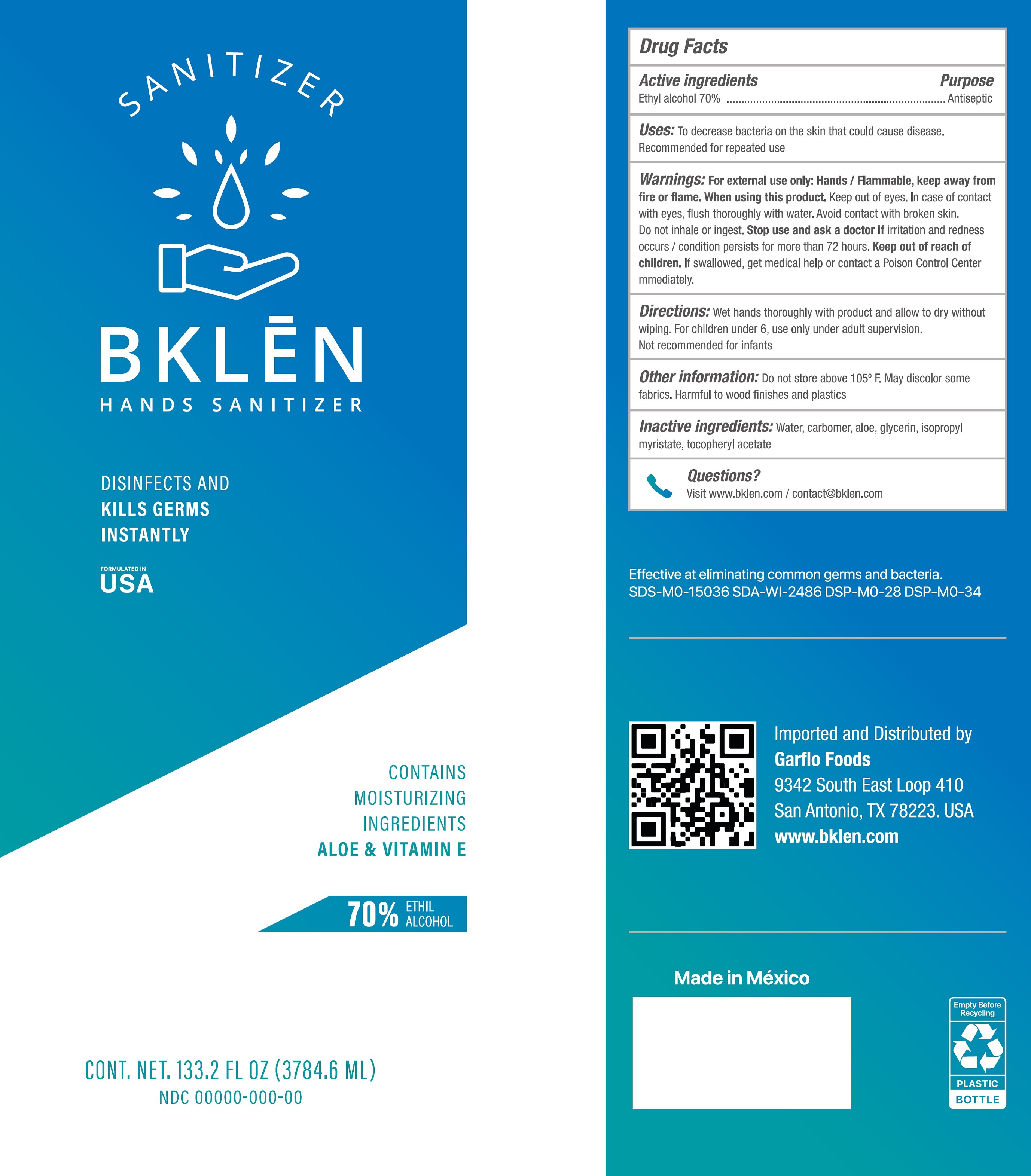 DRUG LABEL: Bklen Hands Sanitizer
NDC: 81081-000 | Form: GEL
Manufacturer: Garflo Inc
Category: otc | Type: HUMAN OTC DRUG LABEL
Date: 20201118

ACTIVE INGREDIENTS: ALCOHOL 0.7 mL/1 mL
INACTIVE INGREDIENTS: WATER; CARBOMER HOMOPOLYMER, UNSPECIFIED TYPE; ALOE VERA LEAF; GLYCERIN; ISOPROPYL MYRISTATE; .ALPHA.-TOCOPHEROL ACETATE

Bklen Hands Sanitizer

Active ingredients

Ethyl alcohol 70%

Purpose

Antiseptic

Uses:

To decrease bacteria on the skin that could cause disease. Recommended for repeated use

Warnings:

For external use only: Hands/ Flammable, keep away from fire or flame.

When using this product:

Keep out of eyes. In case of contact with eyes, flush thoroughly with water/ Avoid contact with broken skin/ Do not inhale or ingest.

Stop use and ask a doctor if

Irritation and redness occurs/ Condition persists for more than 72 hours.

Keep out of reach of children.

If swallowed, get medical help or contact a Poison Control Center immediately.

Directions:

Wet hands thoroughly with product and allow to dry without wiping. For children under 6, use only under adult supervision. Not recommended for infants.

Other information:

Do not store above 105° F. May discolor some fabrics. Harmful to wood finishes and plastics

Inactive ingredients:

Water, carbomer, aloe, glycerin, isopropyl myristate, tocopheryl acetate

Questions?

Visit www.bklen.com / contact@bklen.com